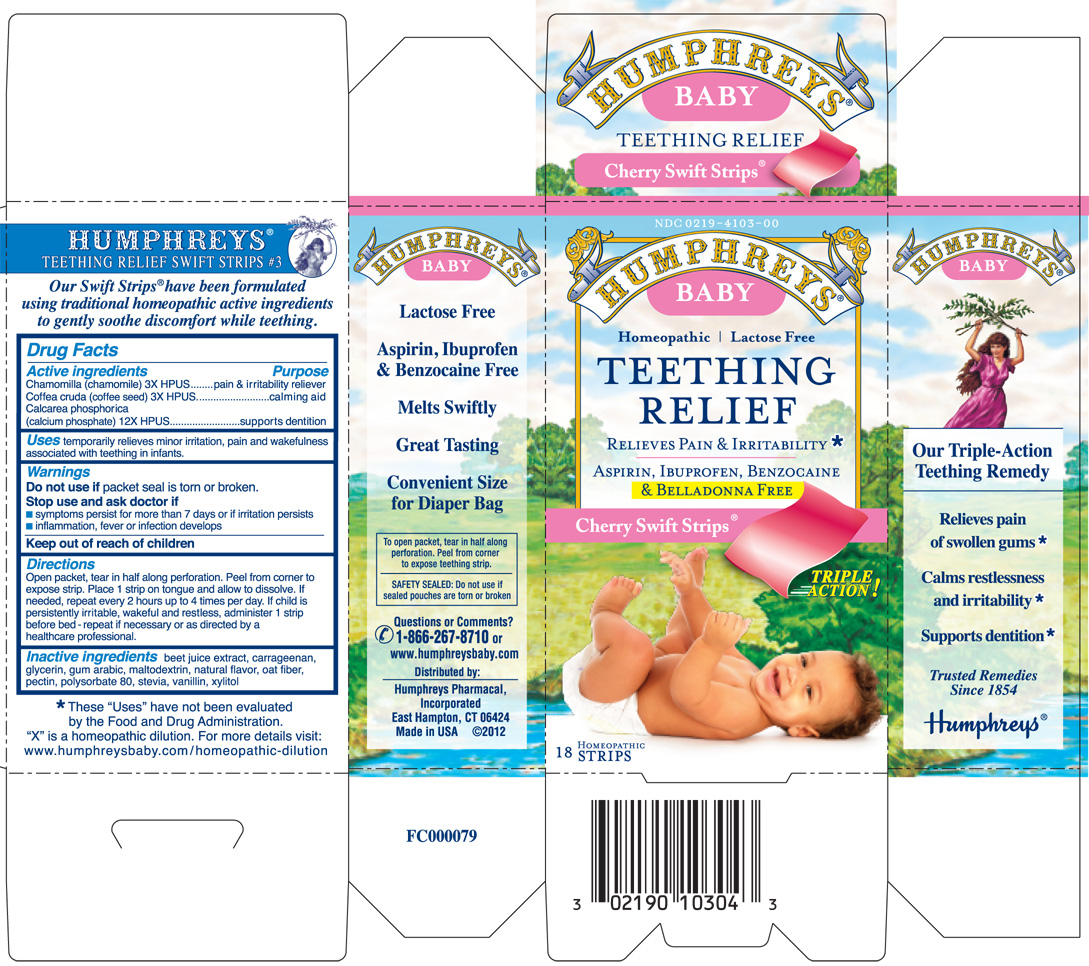 DRUG LABEL: Humphreys Baby Teething Relief Cherry Swift Strips
                
NDC: 0219-4103 | Form: FILM, SOLUBLE
Manufacturer: Humphreys Pharmacal, Incorporated
Category: homeopathic | Type: HUMAN OTC DRUG LABEL
Date: 20120906

ACTIVE INGREDIENTS: matricaria recutita 3 [hp_X]/1 1; arabica coffee bean 3 [hp_X]/1 1; tribasic calcium phosphate 12 [hp_X]/1 1
INACTIVE INGREDIENTS: beet juice; carrageenan; glycerin; acacia; maltodextrin; oat bran; pectin; polysorbate 80; stevia rebaudiuna leaf; vanillin; xylitol

Drug Facts

Active Ingredients:

Chamomilla (chamomile) 3X HPUS

Coffea cruda (coffee seed) 3X HPUS

Calcarea phosphorica (calcium phosphate) 12X HPUS

Purpose

Chamomilla (chamomile) 3X HPUS....................pain & irritability reliever

Coffea cruda (coffee seed) 3X HPUS..................calming aid

Calcarea phosphorica (calcium phosphate) 12X....supports dentition

Uses:

Temporarily relieves minor irritation, pain and wakefulness associated with teething in infants.

Warnings:

Do not use if packet seal is torn or broken.

Stop use and ask doctor if

- symptoms persist for more than 7 days or if irritation persists
- inflammation, fever or infection develops

Keep out of reach of children

Directions:

Open packet, tear in half along perforation. Peel from corner to

expose strip. Place 1 strip on tongue and allow to dissolve. If

needed, repeat every 2 hours up to 4 times per day. If child is

persistently irritable, wakeful and restless, administer 1 strip

before bed - repeat if necessary or as directed by a healthcare professional.

Inactive ingredients

beet juice extract, carrageenan, glycerin, gum arabic, maltodextrin,

natural flavor, oat fiber, pectin, polysorbate 80, stevia, vanillin, xylitol

Questions or Comments?

1-866-267-8710 or

www.humphreysbaby.com

Distributed by: Humphreys Pharmacal, Inc.

East Hampton, CT 06424

Made in USA